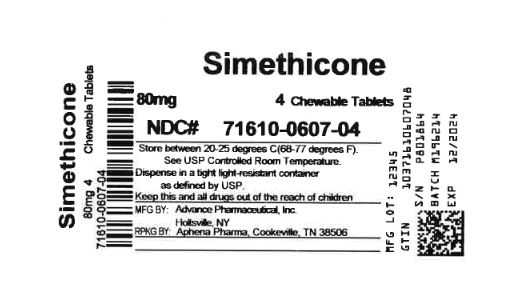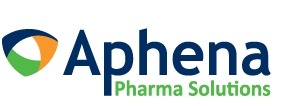 DRUG LABEL: Simethicone
NDC: 71610-607 | Form: TABLET, CHEWABLE
Manufacturer: Aphena Pharma Solutions - Tennessee, LLC
Category: otc | Type: HUMAN OTC DRUG LABEL
Date: 20250109

ACTIVE INGREDIENTS: DIMETHICONE 80 mg/1 1
INACTIVE INGREDIENTS: DEXTROSE; SUCROSE; MALTODEXTRIN; PEPPERMINT; SORBITOL; STEARIC ACID

GAS RELIEF SIMETHICONE

Drug Facts

.

Active Ingredient

(in each chewable tablet)

Simethicone 80 mg

Purpose

Antiflatulent

Uses

relieves

- bloating
- pressure
- discomfort of gas which can be caused by certain foods or air swallowing

Warnings

If pregnant or breast-feeding,ask a health professional before use.

Keep out of reach of children

Directions

- chew thoroughly 1 to 2 tablets as needed after meals and at bed time.
- do not exceed 6 tablets per day unless directed by a doctor

Other Information

- store at room temperature 15-30 °C (59-86 °F)
- protect from moisture

Inactive Ingredients

dextrose, dipac sugar, maltodextrin, peppermint flavor, sorbitol, stearic acid

Questions or Comments

TAMPER EVIDENT: DO NOT USE IF IMPRINTED SAFETY SEAL UNDER CAP IS BROKEN OR MISSING

Call 804-270-4498, 8.30 am – 4.30 pmEST Monday - Friday

Repackaging Information

Please reference the How Suppliedsection listed above for a description of individual tablets. This drug product has been received by Aphena Pharma - TN in a manufacturer or distributor packaged configuration and repackaged in full compliance with all applicable cGMP regulations. The package configurations available from Aphena are listed below:

Count | 80 mg
4 | 71610-607-04

Store between 20°-25°C (68°-77°F). See USP Controlled Room Temperature. Dispense in a tight light-resistant container as defined by USP. Keep this and all drugs out of the reach of children.

Repackaged by:
Cookeville, TN 38506
20211105JH

PRINCIPAL DISPLAY PANEL - 80 mg

NDC 71610-607 - Simethicone 80 mg Chewable Tablets